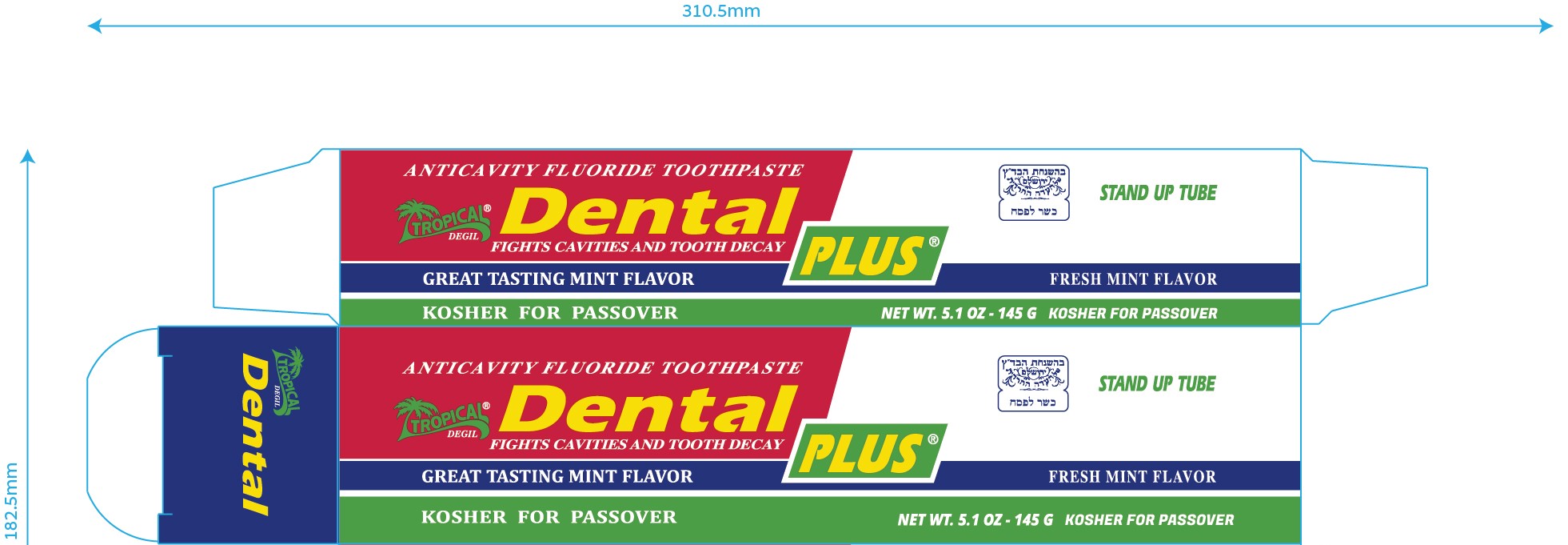 DRUG LABEL: Dental Plus Fresh Mint Flavor
NDC: 62685-218 | Form: PASTE
Manufacturer: tropical degil cosmetics industries ltd
Category: otc | Type: HUMAN OTC DRUG LABEL
Date: 20210223

ACTIVE INGREDIENTS: SODIUM MONOFLUOROPHOSPHATE 1 mg/1 g
INACTIVE INGREDIENTS: SACCHARIN SODIUM; SODIUM BENZOATE; BENZOIC ACID; CALCIUM CARBONATE; SILICON DIOXIDE; SORBITOL; CARBOXYMETHYLCELLULOSE SODIUM; WATER; SODIUM LAURYL SULFATE

Dental Plus Fresh Mint Flavor

Active ingredient

Sodium monofluorophosphate 0.8% (1000 ppm F)

Purpose

Anticavity

Use

Aids in the prevention of dental cavities

Ask a dentist before use if you have

bleeding or redness lasting more than 2 weeks, pain, swelling, pus, loose teeth, or more spacing between teeth. These may be signs of periodontitis, a serious form of gum disease.

Keep out of reach of children under 6 years of age. If more than used for brushing is accidentally swallowed, get medical help or contact a Poison Control Center right away.

Directions

- Adults and children 2 years of age and older: Brush teeth thoroughly, preferrably after each meal or at least twice a day, or as directed by a dentist or doctor. Instruct children under 6 years of age in good brushing and rinsing habits (to minimize swallowing). Supervise children as necessary until capable of using without supervision.
- Children under 2 years of age: Consult a dentist or doctor.

INACTIVE INGREDIENT

Water, sorbitol, calcium carbonate, silica, sodium lauryl sulphate, flavor, cellulose gum, sodium saccharin, sodium benzoate, benzoic acid.

Questions or comments? www.sleeksensation.com

Prinicipal Display Panel

Dental plus fresh mint flavor

anticavity fluoride toothpaste

Net Wt 5.1 oz - 145 g